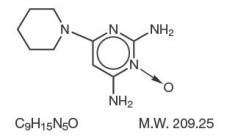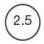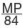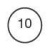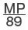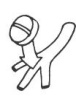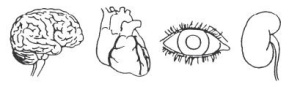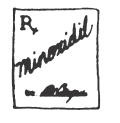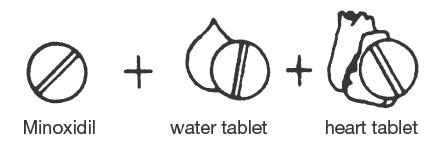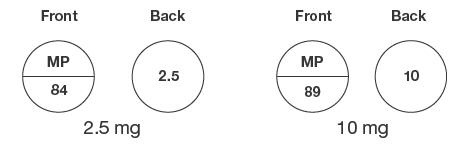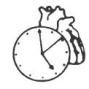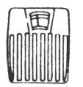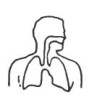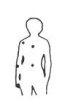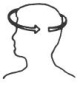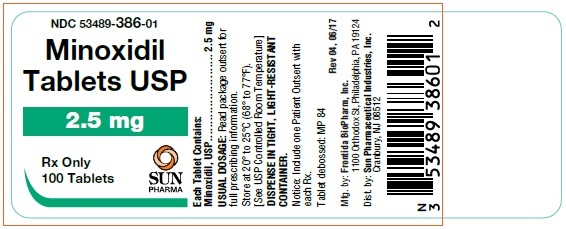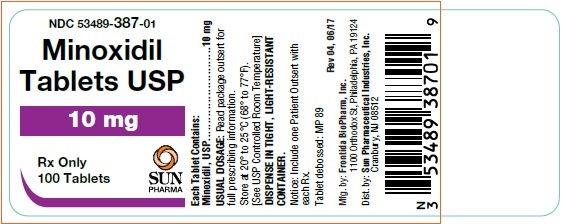 DRUG LABEL: MINOXIDIL
NDC: 53489-386 | Form: TABLET
Manufacturer: Sun Pharmaceutical Industries, Inc.
Category: prescription | Type: HUMAN PRESCRIPTION DRUG LABEL
Date: 20260209

ACTIVE INGREDIENTS: MINOXIDIL 2.5 mg/1 1

MINOXIDIL TABLETS USP

Rx only

WARNINGS

Minoxidil tablets contain the powerful antihypertensive agent, minoxidil, which may produce serious adverse effects. It can cause pericardial effusion, occasionally progressing to tamponade, and angina pectoris may be exacerbated. Minoxidil should be reserved for hypertensive patients who do not respond adequately to maximum therapeutic doses of a diuretic and two other antihypertensive agents.

In experimental animals, minoxidil caused several kinds of myocardial lesions as well as other adverse cardiac effects (see Cardiac Lesions in Animals).

Minoxidil must be administered under close supervision, usually concomitantly with therapeutic doses of a beta-adrenergic blocking agent to prevent tachycardia and increased myocardial workload. It must also usually be given with a diuretic, frequently one acting in the ascending limb of the loop of Henle, to prevent serious fluid accumulation. Patients with malignant hypertension and those already receiving guanethidine (see WARNINGS) should be hospitalized when minoxidil is first administered so that they can be monitored to avoid too rapid, or large orthostatic, decreases in blood pressure.

DESCRIPTION

Minoxidil tablets contain minoxidil, an antihypertensive peripheral vasodilator. Minoxidil occurs as a white to off-white, crystalline powder, soluble in alcohol and propylene glycol; sparingly soluble in methanol; slightly soluble in water; practically insoluble in chloroform, acetone and ethyl acetate. The chemical name for minoxidil is 2,4-Pyrimidinediamine, 6-(1-piperidinyl)-, 3-oxide. The structural formula is represented below:

Minoxidil tablets for oral administration contain either 2.5 mg or 10 mg of minoxidil. Inactive ingredients: anhydrous lactose, colloidal silicon dioxide, magnesium stearate, microcrystalline cellulose, and sodium starch glycolate.

CLINICAL PHARMACOLOGY

1. General Pharmacologic Properties

Minoxidil is an orally effective direct acting peripheral vasodilator that reduces elevated systolic and diastolic blood pressure by decreasing peripheral vascular resistance. Microcirculatory blood flow in animals is enhanced or maintained in all systemic vascular beds. In man, forearm and renal vascular resistance decline; forearm blood flow increases while renal blood flow and glomerular filtration rate are preserved.

Because it causes peripheral vasodilation, minoxidil elicits a number of predictable reactions. Reduction of peripheral arteriolar resistance and the associated fall in blood pressure trigger sympathetic, vagal inhibitory, and renal homeostatic mechanisms, including an increase in renin secretion, that lead to increased cardiac rate and output and salt and water retention. These adverse effects can usually be minimized by concomitant administration of a diuretic and a beta-adrenergic blocking agent or other sympathetic nervous system suppressant.

Minoxidil does not interfere with vasomotor reflexes and therefore does not produce orthostatic hypotension. The drug does not enter the central nervous system in experimental animals in significant amounts, and it does not affect CNS function in man.

2. Effects on Blood Pressure and Target Organs

The extent and time-course of blood pressure reduction by minoxidil do not correspond closely to its concentration in plasma. After an effective single oral dose, blood pressure usually starts to decline within one-half hour, reaches a minimum between 2 and 3 hours and recovers at an arithmetically linear rate of about 30%/day. The total duration of effect is approximately 75 hours. When minoxidil is administered chronically, once or twice a day, the time required to achieve maximum effect on blood pressure with a given daily dose is inversely related to the size of the dose. Thus, maximum effect is achieved on 10 mg/day within 7 days, on 20 mg/day within 5 days, and on 40 mg/day within 3 days.

The blood pressure response to minoxidil is linearly related to the logarithm of the dose administered. The slope of this log-linear dose-response relationship is proportional to the extent of hypertension and approaches zero at a supine diastolic blood pressure of approximately 85 mm Hg.

When used in severely hypertensive patients resistant to other therapy, frequently with an accompanying diuretic and beta-blocker, minoxidil tablets usually decreased the blood pressure and reversed encephalopathy and retinopathy.

3. Absorption and Metabolism

Minoxidil is at least 90% absorbed from the Gl tract in experimental animals and man. Plasma levels of the parent drug reach maximum within the first hour and decline rapidly thereafter. The average plasma half-life in man is 4.2 hours. Approximately 90% of the administered drug is metabolized, predominantly by conjugation with glucuronic acid at the N-oxide position in the pyrimidine ring, but also by conversion to more polar products. Known metabolites exert much less pharmacologic effect than minoxidil itself; all are excreted principally in the urine. Minoxidil does not bind to plasma proteins, and does not cross the bloood brain barrier. Its renal clearance corresponds to the glomerular filtration rate. In the absence of functional renal tissue, minoxidil and its metabolites can be removed by hemodialysis.

4. Cardiac Lesions in Animals

Minoxidil produces several cardiac lesions in animals. Some are characteristic of agents that cause tachycardia and diastolic hypotension (beta-agonists like isoproterenol, arterial dilators like hydralazine) while others are produced by a narrower range of agents with arterial dilating properties. The significance of these lesions for humans is not clear, as they have not been recognized in patients treated with oral minoxidil at systemically active doses, despite formal review of over 150 autopsies of treated patients.

(a) Papillary muscle/subendocardial necrosis
The most characteristic lesion of minoxidil, seen in rat, dog, and minipig (but not monkeys) is focal necrosis of the papillary muscle and subendocardial areas of the left ventricle. These lesions appear rapidly, within a few days of treatment with doses of 0.5 to 10 mg/kg/day in the dog and minipig, and are not progressive, although they leave residual scars. They are similar to lesions produced by other peripheral arterial dilators, by theobromine, and by beta-adrenergic receptor agonists such as isoproterenol, epinephrine, and albuterol. The lesions are thought to reflect ischemia provoked by increased oxygen demand (tachycardia, increased cardiac output) and relative decrease in coronary flow (decreased diastolic pressure and decreased time in diastole) caused by the vasodilatory effects of these agents coupled with reflex or directly induced tachycardia.

(b) Hemorrhagic lesions
After acute oral minoxidil treatment (0.5 to 10 mg/kg/day) in dogs and minipigs, hemorrhagic lesions are seen in many parts of the heart, mainly in the epicardium, endocardium, and walls of small coronary arteries and arterioles. In minipigs the lesions occur primarily in the left atrium while in dogs they are most prominent in the right atrium, frequently appearing as grossly visible hemorrhagic lesions. With exposure of 1–20 mg/kg/day in the dog for 30 days or longer, there is replacement of myocardial cells by proliferating fibroblasts and angioblasts, hemorrhage and hemosiderin accumulation. These lesions can be produced by topical minoxidil administration that gives systemic absorption of 0.5 to 1 mg/kg/day. Other peripheral dilators, including an experimental agent, nicorandil, and theobromine, have produced similar lesions.

(c) Epicarditis
A less fully studied lesion is focal epicarditis, seen in dogs after 2 days of oral minoxidil. More recently, chronic proliferative epicarditis was observed in dogs treated topically twice a day for 90 days. In a one year oral dog study, serosanguinous pericardial fluid was seen.

(d) Hypertrophy and Dilation
Oral and topical studies in rats, dogs, monkeys (oral only), and rabbits (dermal only) show cardiac hypertrophy and dilation. This is presumed to represent the consequences of prolonged fluid overload; there is preliminary evidence in monkeys that diuretics partly reverse these effects.

Autopsies of over 150 patients who died of various causes after receiving minoxidil for hypertension have not revealed the characteristic hemorrhagic (especially atrial) lesions seen in dogs and minipigs. While areas of papillary muscle and subendocardial necrosis were occasionally seen, they occurred in the presence of known pre-existing coronary artery disease and were also seen in patients never exposed to minoxidil in another series using similar, but not identical, autopsy methods.

INDICATIONS AND USAGE

Because of the potential for serious adverse effects, minoxidil tablets are indicated only in the treatment of hypertension that is symptomatic or associated with target organ damage and is not manageable with maximum therapeutic doses of a diuretic plus two other antihypertensive drugs. At the present time use in milder degrees of hypertension is not recommended because the benefit-risk relationship in such patients has not been defined.

Minoxidil reduced supine diastolic blood pressure by 20 mm Hg or to 90 mm Hg or less in approximately 75% of patients, most of who had hypertension that could not be controlled by other drugs.

CONTRAINDICATIONS

Minoxidil tablets are contraindicated in pheochromocytoma, because it may stimulate secretion of catecholamines from the tumor through its antihypertensive action. Minoxidil tablets are contraindicated in those patients with a history of hypersensitivity to any of the components of the preparation.

WARNINGS

1. Salt and Water Retention

Congestive Heart Failure — concomitant use of an adequate diuretic is required — Minoxidil tablets must usually be administered concomitantly with a diuretic adequate to prevent fluid retention and possible congestive heart failure; a high ceiling (loop) diuretic is almost alwaysrequired. Body weight should be monitored closely. If minoxidil is used without a diuretic, retention of several hundred milliequivalents of salt and corresponding volumes of water can occur within a few days, leading to increased plasma and interstitial fluid volume and local or generalized edema. Diuretic treatment alone, or in combination with restricted salt intake, will usually minimize fluid retention, although reversible edema did develop in approximately 10% of nondialysis patients so treated. Ascites has also been reported. Diuretic effectiveness was limited mostly by disease-related impaired renal function. The condition of patients with pre-existing congestive heart failure occasionally deteriorated in association with fluid retention although because of the fall in blood pressure (reduction of afterload), more than twice as many improved than worsened. Rarely, refractory fluid retention may require discontinuation of minoxidil. Provided that the patient is under close medical supervision, it may be possible to resolve refractory salt retention by discontinuing minoxidil for 1 or 2 days and then resuming treatment in conjunction with vigorous diuretic therapy.

2. Concomitant Treatment to Prevent Tachycardia is Usually Required

Minoxidil increases the heart rate. Angina may worsen or appear for the first time during minoxidil treatment, probably because of the increased oxygen demands associated with increased heart rate and cardiac output. The increase in rate and the occurrence of angina generally can be prevented by the concomitant administration of a beta-adrenergic blocking drug or other sympathetic nervous system suppressant. The ability of beta-adrenergic blocking agents to minimize papillary muscle lesions in animals is further reason to utilize such an agent concomitantly. Round-the-clock effectiveness of the sympathetic suppressant should be ensured.

3. Pericarditis, Pericardial Effusion and Tamponade

There have been reports of pericarditis occurring in association with the use of minoxidil. The relationship of this association to renal status is uncertain. Pericardial effusion, occasionally with tamponade, has been observed in about 3% of treated patients not on dialysis, especially those with inadequate or compromised renal function. Although in many cases, the pericardial effusion was associated with a connective tissue disease, the uremic syndrome, congestive heart failure, or marked fluid retention, there have been instances in which these potential causes of effusion were not present. Patients should be observed closely for any suggestion of a pericardial disorder, and echocardiographic studies should be carried out if suspicion arises. More vigorous diuretic therapy, dialysis, pericardiocentesis, or surgery may be required. If the effusion persists, withdrawal of minoxidil should be considered in light of other means of controlling the hypertension and the patient's clinical status.

4. Interaction with Guanethidine

Although minoxidil does not itself cause orthostatic hypotension, its administration to patients already receiving guanethidine can result in profound orthostatic effects. If at all possible, guanethidine should be discontinued well before minoxidil is begun. Where this is not possible, minoxidil therapy should be started in the hospital and the patient should remain institutionalized until severe orthostatic effects are no longer present or the patient has learned to avoid activities that provoke them.

5. Hazard of Rapid Control of Blood Pressure

In patients with very severe blood pressure elevation, too rapid control of blood pressure, especially with intravenous agents, can precipitate syncope, cerebrovascular accidents, myocardial infarction and ischemia of special sense organs with resulting decrease or loss of vision or hearing. Patients with compromised circulation or cryoglobulinemia may also suffer ischemic episodes of the affected organs. Although such events have not been unequivocally associated with minoxidil use, total experience is limited at present.

Any patient with malignant hypertension should have initial treatment with minoxidil carried out in a hospital setting, both to assure that blood pressure is falling and to assure that it is not falling more rapidly than intended.

PRECAUTIONS

1. General Precautions

(a) Monitor fluid and electrolyte balance and body weight (see WARNINGS: Salt and Water Retention).

(b) Observe patients for signs and symptoms of pericardial effusion (see WARNINGS: Pericarditis, Pericardial Effusion, and Tamponade).

(c) Use after myocardial infarction— Minoxidil tablets have not been used in patients who have had a myocardial infarction within the preceding month. It is possible that a reduction of arterial pressure with minoxidil might further limit blood flow to the myocardium, although this might be compensated by decreased oxygen demand because of lower blood pressure.

(d) Hypersensitivity— Possible hypersensitivity to minoxidil, manifested as a skin rash, has been seen in less than 1% of patients; whether the drug should be discontinued when this occurs depends on treatment alternatives.

(e) Renal failure or dialysispatients may require smaller doses of minoxidil and should have close medical supervision to prevent exacerbation of renal failure or precipitation of cardiac failure.

2. Information for patient

The patient should be fully aware of the importance of continuing all of his antihypertensive medications and of the nature of symptoms that would suggest fluid overload. A patient brochure has been prepared and is included with each minoxidil package. The text of this brochure is reprinted at the end of the insert.

3. Laboratory tests

Those laboratory tests which are abnormal at the time of initiation of minoxidil therapy, such as urinalysis, renal function tests, EKG, chest x-ray, echocardiogram, etc., should be repeated at intervals to ascertain whether improvement or deterioration is occurring under minoxidil therapy. Initially such tests should be performed frequently, e.g., 1–3 month intervals; later as stabilization occurs, at intervals of 6–12 months.

4. Drug interactions

See “Interaction with Guanethidine” under WARNINGS.

5. Carcinogenesis, Mutagenesis, Impairment of Fertility

Two-year carcinogenicity studies of minoxidil have been conducted by the dermal and oral (dietary) routes of administration in mice and rats. There were no positive findings with the oral (dietary) route of administration in rats.

In the two-year dermal study in mice, an increased incidence of mammary adenomas and adenocarcinomas in the females at all dose levels (8, 25 and 80 mg/kg/day) was attributed to increased prolactin activity. Hyperprolactinemia is a well-known mechanism in the enhancement of mouse mammary tumors, but has not been associated with mammary tumorigenesis in women. Additionally, topical minoxidil has not been shown to cause hyperprolactinemia in women on clinical trials. Absorption of minoxidil through rodent skin is greater than would be experienced by patients treated topically with minoxidil for hair loss. Dietary administration of minoxidil to mice for up to 2 years was associated with an increased incidence of malignant lymphomas in females at all dose levels (10, 25 and 63 mg/kg/day) and an increased incidence of hepatic nodules in males (63 mg/kg/day). There was no effect of dietary minoxidil on the incidence of malignant liver tumors.

In the two-year dermal study in rats there were significant increases in incidence of pheochromocytomas in males and females and preputial gland adenomas in males. Changes in incidence of neoplasms found to be increased in the dermal or oral carcinogenicity studies were typical of those expected in rodents treated with other hypotensive agents (adrenal pheochromocytomas in rats), treatment-related hormonal alterations (mammary carcinomas in female mice; preputial gland adenomas in male rats) or representative of normal variations within the range of historical incidence for rodent neoplasms (malignant lymphomas, liver nodules/adenomas in mice). Based on differences in absorption of minoxidil and mechanisms of tumorigenesis in these rodent species, none of these changes were considered to be relevant to the safety of patients treated topically with minoxidil for hair loss.

There was no evidence of epithelial hyperplasia or tumorigenesis at the sites of topical application of minoxidil in either species in the two-year dermal carcinogenesis studies. No evidence of carcinogenicity was detected in rats or rabbits treated topically with minoxidil for one year. Topical minoxidil (2% and 5%) did not significantly (p < 0.05) reduce the latency period of UV light-initiated skin tumors in hairless mice, as compared to controls, in a 12-month photocarcinogenicity study.

Minoxidil was not mutagenic in the Salmonella(Ames) test, the DNA damage alkaline elution assay, the in vitrorat hepatocyte unscheduled DNA synthesis (UDS) assay, the rat bone marrow micronucleus assay, or the mouse bone marrow micronucleus assay. An equivocal result was recorded in an in vitrocytogenetic assay using Chinese hamster cells at long exposure times, but a similar assay using human lymphocytes was negative.

In a study in which male and female rats received one or five times the maximum recommended human oral antihypertensive dose of minoxidil (multiples based on a 50 kg patient) there was a dose-dependent reduction in conception rate.

6. Pregnancy

Teratogenic Effects

Pregnancy Category C. Oral administration of minoxidil has been associated with evidence of increased fetal resorption in rabbits, but not rats, when administered at five times the maximum recommended oral antihypertensive human dose. There was no evidence of teratogenic effects in rats and rabbits. Subcutaneous administration of minoxidil to pregnant rats at 80 mg/kg/day was maternally toxic but not teratogenic. Higher subcutaneous doses produced evidence of developmental toxicity. There are no adequate and well controlled studies in pregnant women. Minoxidil should be used during pregnancy only if the potential benefit justifies the potential risk to the fetus. Neonatal hypertrichosis has been reported following exposure to minoxidil during pregnancy.

7. Labor and Delivery

The effects on labor and delivery are unknown.

8. Nursing Mothers

There has been one report of minoxidil excretion in the breast milk of a woman treated with 5 mg oral minoxidil twice daily for hypertension. Because of the potential for adverse effects in nursing infants from minoxidil absorption minoxidil should not be administered to a nursing woman.

9. Pediatric Use

Use in pediatric patients has been limited to date, particularly in infants. The recommendations under DOSAGE AND ADMINISTRATION can be considered only a rough guide at present and a careful titration is essential.

10. Geriatric Use

Clinical studies of minoxidil tablets did not include sufficient numbers of subjects aged 65 and over to determine whether they respond differently from younger subjects. Other reported clinical experience has not identified differences in responses between the elderly and younger patients. In general, dose selection for an elderly patient should be cautious, usually starting at the low end of the dosing range, reflecting the greater frequency of decreased hepatic, renal, or cardiac function, and of concomitant disease or other drug therapy.

11. Unapproved Use

Use of minoxidil tablets, in any formulation, to promote hair growth is not an approved indication. While clinical trials with minoxidil topical solution 2% demonstrated that formulation and dosage were safe and effective, the effects of extemporaneous formulations and dosages have not been shown to be safe or effective. Because systemic absorption of topically applied drug may occur and is dependent on vehicle and/or method of use, extemporaneous topical formulations made from minoxidil should be considered to share in the full range of CONTRAINDICATIONS, WARNINGS, PRECAUTIONS, and ADVERSE REACTIONS listed in this insert. In addition, skin intolerance to drug and/or vehicle may occur.

ADVERSE REACTIONS

1. Salt and Water Retention (see WARNINGS: Concomitant Use of Adequate Diuretic is Required) — Temporary edema developed in 7% of patients who were not edematous at the start of therapy.

2. Pericarditis, Pericardial Effusion and Tamponade (see WARNINGS).

3. Dermatologic— Hypertrichosis— Elongation, thickening, and enhanced pigmentation of fine body hair are seen in about 80% of patients taking minoxidil tablets. This develops within 3 to 6 weeks after starting therapy. It is usually first noticed on the temples, between the eyebrows, between the hairline and the eyebrows, or in the side-burn area of the upper lateral cheek, later extending to the back, arms, legs, and scalp. Upon discontinuation of minoxidil, new hair growth stops, but 1 to 6 months may be required for restoration to pretreatment appearance. No endocrine abnormalities have been found to explain the abnormal hair growth; thus, it is hypertrichosis without virilism. Hair growth is especially disturbing to children and women and such patients should be thoroughly informed about this effect before therapy with minoxidil is begun.

Allergic— Rashes have been reported, including rare reports of bullous eruptions, toxic epidermal necrolysis, and Stevens-Johnson Syndrome.

4. Hematologic— Thrombocytopenia and leukopenia (WBC<3000/mm^3) have rarely been reported.

5. Gastrointestinal— Nausea and/or vomiting has been reported. In clinical trials the incidence of nausea and vomiting associated with the underlying disease has shown a decrease from pretrial levels.

6. Miscellaneous— Breast tenderness — This developed in less than 1 % of patients.

7. Altered Laboratory Findings— (a) ECG changes— Changes in direction and magnitude of the ECG T-waves occur in approximately 60% of patients treated with minoxidil. In rare instances a large negative amplitude of the T-wave may encroach upon the S-T segment, but the S-T segment is not independently altered. These changes usually disappear with continuance of treatment and revert to the pretreatment state if minoxidil is discontinued. No symptoms have been associated with these changes, nor have there been alterations in blood cell counts or in plasma enzyme concentrations that would suggest myocardial damage. Long-term treatment of patients manifesting such changes has provided no evidence of deteriorating cardiac function. At present the changes appear to be nonspecific and without identifiable clinical significance. (b) Effects of hemodilution— hematocrit, hemoglobin and erythrocyte count usually fall about 7% initially and then recover to pretreatment levels. (c) Other— Alkaline phosphatase increased varyingly without other evidence of liver or bone abnormality. Serum creatinine increased an average of 6% and BUN slightly more, but later declined to pretreatment levels.

OVERDOSAGE

There have been only a few instances of deliberate or accidental overdosage with minoxidil tablets. One patient recovered after taking 50 mg of minoxidil together with 500 mg of a barbiturate. When exaggerated hypotension is encountered, it is most likely to occur in association with residual sympathetic nervous system blockade from previous therapy (guanethidine-like effects or alpha-adrenergic blockage), which prevents the usual compensatory maintenance of blood pressure. Intravenous administration of normal saline will help to maintain blood pressure and facilitate urine formation in these patients. Sympathomimetic drugs such as norepinephrine or epinephrine should be avoided because of their excessive cardiac stimulating action. Phenylephrine, angiotensin II, vasopressin, and dopamine all reverse hypotension due to minoxidil, but should only be used if underperfusion of a vital organ is evident.

Radioimmunoassay can be performed to determine the concentration of minoxidil in the blood. At the maximum adult dose of 100 mg/day, peak blood levels of 1641 ng/mL and 2441 ng/mL were observed in two patients, respectively. Due to patient-to-patient variation in blood levels, it is difficult to establish an overdosage warning level. In general, a substantial increase above 2000 ng/mL should be regarded as overdosage, unless the physician is aware that the patient has taken no more than the maximum dose.

Oral LD50 in rats has ranged from 1321–3492 mg/kg; in mice, 2456–2648 mg/kg.

DOSAGE AND ADMINISTRATION

Patients over 12 years of age: The recommended initial dosage of minoxidil tablets is 5 mg of minoxidil given as a single daily dose. Daily dosage can be increased to 10, 20 and then to 40 mg in single or divided doses if required for optimum blood pressure control. The effective dosage range is usually 10 to 40 mg per day. The maximum recommended dosage is 100 mg per day.

Patients under 12 years of age: The initial dosage is 0.2 mg/kg minoxidil as a single daily dose. The dosage may be increased in 50 to 100% increments until optimum blood pressure control is achieved. The effective dosage range is usually 0.25 mg to 1 mg/kg/day. The maximum recommended dosage is 50 mg daily (see 9. Pediatric Useunder PRECAUTIONS).

Dose frequency: The magnitude of within-day fluctuation of arterial pressure during therapy with minoxidil is directly proportional to the extent of pressure reduction. If supine diastolic pressure has been reduced less than 30 mm Hg, the drug need be administered only once a day; if supine diastolic pressure has been reduced more than 30 mm Hg, the daily dosage should be divided into two equal parts.

Frequency of dosage adjustment: Dosage must be titrated carefully according to individual response. Intervals between dosage adjustments normally should be at least 3 days since the full response to a given dose is not obtained for at least that amount of time. Where a more rapid management of hypertension is required, dose adjustments can be made every 6 hours if the patient is carefully monitored.

Concomitant therapy: Diuretic and beta-blocker or other sympathetic nervous system suppressant.

Diuretics:Minoxidil must be used in conjunction with a diuretic in patients relying on renal function for maintaining salt and water balance. Diuretics have been used at the following dosages when starting therapy with minoxidil: hydrochlorothiazide (50 mg, b.i.d.) or other thiazides at equieffective dosage; chlorthalidone (50 to 100 mg, once daily); furosemide (40 mg, b.i.d.). If excessive salt and water retention results in a weight gain of more than 5 pounds, diuretic therapy should be changed to furosemide; if the patient is already taking furosemide, dosage should be increased in accordance with the patient's requirements.

Beta-blocker or other sympathetic nervous system suppressants: When therapy with minoxidil is begun, the dosage of a beta-adrenergic receptor blocking drug should be the equivalent of 80 to 160 mg of propranolol per day in divided doses.

If beta-blockers are contraindicated, methyldopa (250 to 750 mg, b.i.d.) may be used instead. Methyldopa must be given for at least 24 hours before starting therapy with minoxidil because of the delay in the onset of methyldopa's action. Limited clinical experience indicates that clonidine may also be used to prevent tachycardia induced by minoxidil; the usual dosage is 0.1 to 0.2 mg twice daily.

Sympathetic nervous system suppressants may not completely prevent an increase in heart rate due to minoxidil but usually do prevent tachycardia. Typically, patients receiving a beta-blocker prior to initiation of therapy with minoxidil have a bradycardia and can be expected to have an increase in heart rate toward normal when minoxidil is added. When treatment with minoxidil and beta-blocker or other sympathetic nervous system suppressant are begun simultaneously, their opposing cardiac effects usually nullify each other, leading to little change in heart rate.

HOW SUPPLIED

Minoxidil tablets are available as follows:

Minoxidil tablets 2.5 mg are round, scored, white and debossed on one side and on the reverse side.

Bottles of 100 | NDC 53489-386-01
Bottles of 250 | NDC 53489-386-03
Bottles of 500 | NDC 53489-386-05
Bottles of 1000 | NDC 53489-386-10

Minoxidil tablets 10 mg are round, scored, white and debossed on one side and on the reverse side.

Bottles of 100 | NDC 53489-387-01
Bottles of 250 | NDC 53489-387-03
Bottles of 500 | NDC 53489-387-05
Bottles of 1000 | NDC 53489-387-10

STORAGE AND HANDLING

Store at 20° to 25°C (68° to 77° F). [See USP Controlled Room Temperature]
DISPENSE IN TIGHT, LIGHT-RESISTANT CONTAINER.

PATIENT INFORMATION

Minoxidil tablets contain minoxidil, a medicine for the treatment of high blood pressure in the patient who has not been controlled or is experiencing unacceptable side effects with other medications. It must usually be taken with other medicines.

Be absolutely sure to take all of your medicines for high blood pressure according to your doctor's instructions. Do not stop taking minoxidil unless your doctor tells you to. Do not give any of your medicine to other people.

It is important that you look for the warning signals of certain undesired effects of minoxidil. Call your doctor if they occur. Your doctor will need to see you regularly while you are taking minoxidil. Be sure to keep all your appointments or to arrange for new ones if you must miss one.

Do not hesitate to call your doctor if any discomforts or problems occur.

The information here is intended to help you take minoxidil properly. It does not tell you all there is to know about minoxidil. There is a more technical leaflet that you may request from the pharmacist; you may need your doctor's help in understanding parts of that leaflet.

What is Minoxidil?

Minoxidil tablets contain minoxidil which is a drug for lowering the blood pressure. It works by relaxing and enlarging certain small blood vessels so that blood flows through them more easily.

Why lower blood pressure?

Your doctor has prescribed minoxidil to lower your blood pressure and protect vital parts of your body. Uncontrolled blood pressure can cause stroke, heart failure, blindness, kidney failure and heart attacks.

Most people with high blood pressure need to take medicines to treat it for their whole lives.

Who should take Minoxidil tablets?

There are many people with high blood pressure, but most of them do not need minoxidil. Minoxidil is used ONLY when your doctor decides that:

1. your high blood pressure is severe;
2. your high blood pressure is causing symptoms or damage to vital organs; and
3. other medicines did not work well enough or had very disturbing side effects.

Minoxidil should be taken only when a doctor prescribes it. Never give any of your minoxidil tablets, or any other high blood pressure medicine, to a friend or relative.

Pregnancy: In some cases doctors may prescribe minoxidil for women who are pregnant or who are planning to have children. However, its safe use in pregnancy has not been established. Laboratory animals had a reduced ability to become pregnant and a reduced survival of offspring while taking minoxidil. If you are pregnant or are planning to become pregnant, be sure to tell your doctor.

How to take Minoxidil tablets.

Usually, your doctor will prescribe two other medicines along with minoxidil. These will help lower blood pressure and will help prevent undesired effects of minoxidil.

Often, when a medicine like minoxidil lowers blood pressure, your body tries to return the blood pressure to the original higher level. It does this by holding on to water and salt (so there will be more fluid to pump) and by making your heart beat faster. To prevent this, your doctor will usually prescribe a water tablet to remove the extra salt and water from your body (a diuretic: dye-u-RET-tic) and another medicine to slow your heart beat.

You must follow your doctor's instructions exactly, taking all the prescribed medicines, in the right amounts, each day.These medicines will help keep your blood pressure down. The water tablet and heart beat medicine will help prevent the undesired effects of minoxidil.

Minoxidil tablets come in two strengths (2.5 milligrams and 10 milligrams) that are marked on each tablet. Pay close attention to the tablet markings to be sure you are taking the correct strength. Your doctor may prescribe half a tablet; the tablets are scored (partly cut on one side) so that you can easily break them.

When you first start taking minoxidil, your doctor may need to see you often in order to adjust your dosage. Take all your medicine according to the schedule prescribed by your doctor. Do not skip any doses. If you should forget a dose of minoxidil, wait until it is time for your next dose, then continue with your regular schedule. Remember: do not stop taking minoxidil, or any of your other high blood pressure medicines, without checking with your doctor.Make sure that any doctor treating or examining you knows that you are taking high blood pressure medicines, including minoxidil.

WARNING SIGNALS

Even if you take all your medicines correctly, minoxidil tablets may cause undesired effects. Some of these are serious and you should be on the lookout for them. If any of the following warning signals occur, you must call your doctor immediately:

1. Increase in heart rate— You should measure your heart rate by counting your pulse rate while you are resting. If you have an increase of 20 beats or more a minute over your normal pulse, contact your doctor immediately. If you do not know how to take your pulse rate, ask your doctor. Also ask your doctor how often to check your pulse.

2. Rapid weight gain of more than 5 pounds— You should weigh yourself daily. If you quickly gain five or more pounds, or if there is any swelling or puffiness in the face, hands, ankles, or stomach area, this could be a sign that you are retaining body fluids. Your doctor may have to change your drugs or change the dose of your drugs. You may also need to reduce the amount of salt you eat. A smaller weight gain (2 to 3 pounds) often occurs when treatment is started. You may lose this extra weight with continued treatment.

3. Increased difficulty in breathing,especially when lying down. This too may be due to an increase of body fluids. It can also happen because your high blood pressure is getting worse. In either case, you might require treatment with other medicines.

4. New or worsening of pain in the chest, arm, or shoulder or signs of severe indigestion— These could be signs of serious heart problems.

5. Dizziness, lightheadedness or fainting— These can be signs of high blood pressure or they may be side effects from one of the medicines. Your doctor may need to change or adjust the dosage of the medicines you are taking.

OTHER UNDESIRED EFFECTS

Minoxidil tablets can cause other undesired effects such as nausea and/or vomiting that are annoying but not dangerous. Do not stop taking the drug because of these other undesired effects without talking to your doctor.

Hair growth: About 8 out of every 10 patients who have taken minoxidil noticed that fine body hair grew darker or longer on certain parts of the body. This happened about 3 to 6 weeks after beginning treatment. The hair may first be noticed on the forehead and temples, between the eyebrows, or on the upper part of the cheeks. Later, hair may grow on the back, arms, legs, or scalp. Although hair growth may not be noticeable to some patients, it often is bothersome in women and children. Unwanted hair can be controlled with a hair remover or by shaving. The extra hair is not permanent, it disappears within 1 to 6 months of stopping minoxidil. Nevertheless, you should not stop taking minoxidil without first talking to your doctor.

A few patients have developed a rash or breast tenderness while taking minoxidil tablets, but this is unusual.

Distributed by:
Sun Pharmaceutical Industries, Inc.
Cranbury, NJ 08512

Rev 03, August 2016